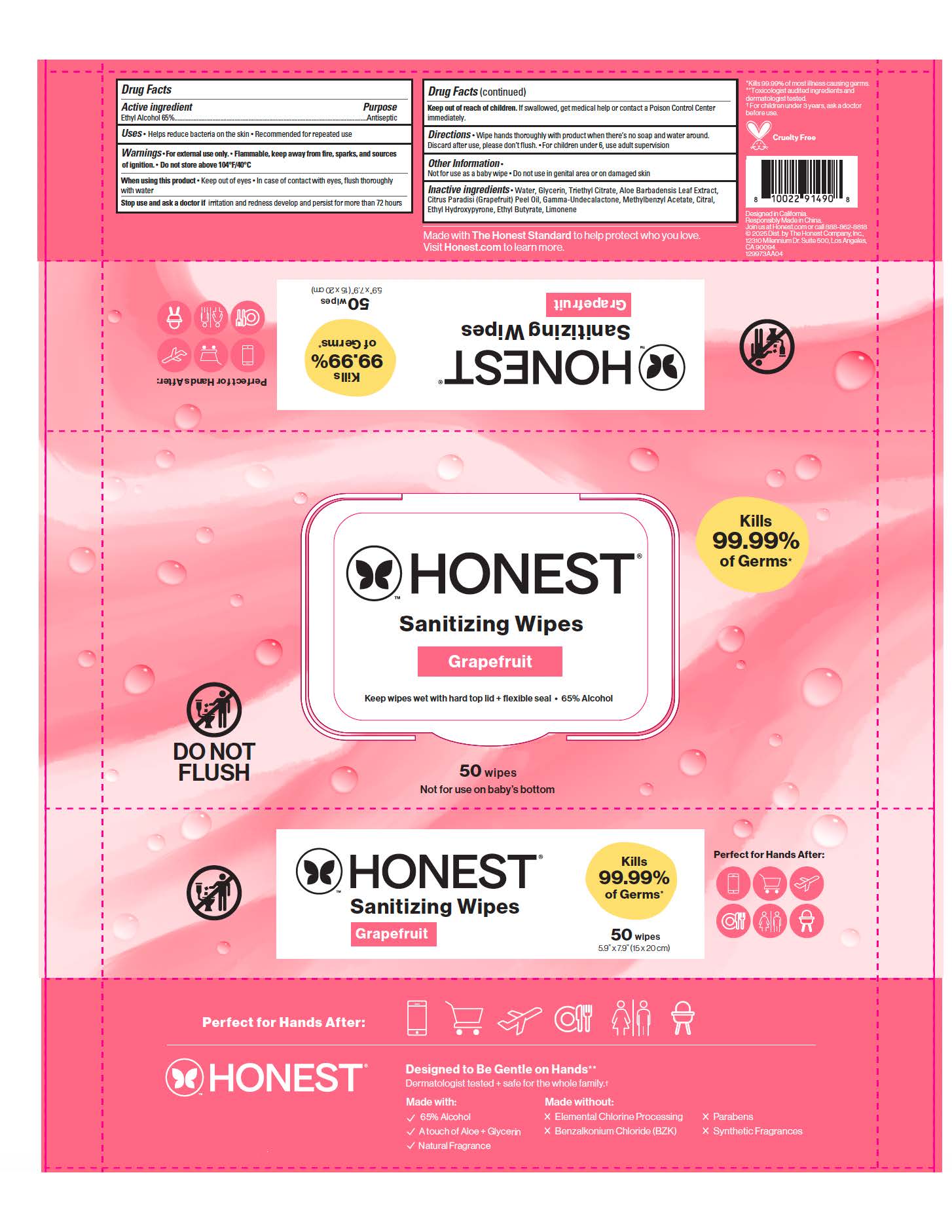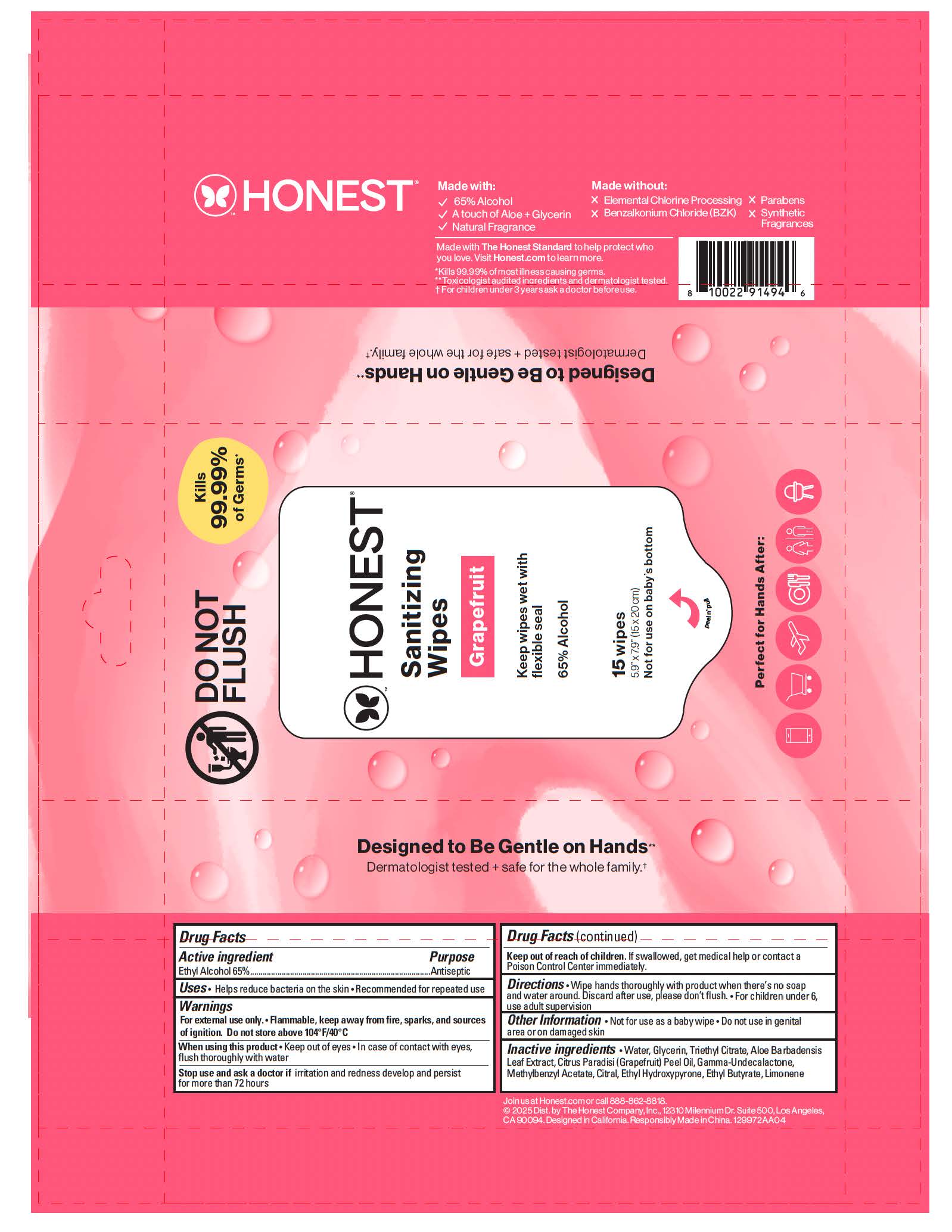 DRUG LABEL: Sanitizing Wipes Grapefruit
NDC: 69366-320 | Form: CLOTH
Manufacturer: The Honest Company Inc.
Category: otc | Type: HUMAN OTC DRUG LABEL
Date: 20260212

ACTIVE INGREDIENTS: ALCOHOL 65 mL/100 mL
INACTIVE INGREDIENTS: METHYLBENZYL ACETATE; TRIETHYL CITRATE; GLYCERIN; GAMMA-UNDECALACTONE; LIMONENE, (+)-; CITRUS PARADISI (GRAPEFRUIT) PEEL OIL; WATER; ALOE BARBADENSIS LEAF; ETHYL BUTYRATE; CITRAL; ETHYL HYDROXYPYRONE

Sanitizing Wipes Grapefruit

Active ingredient

Ethyl Alcohol 65%

Directions

• Wipe hands thoroughly with product when there’s no soap and water around. Discard after use, please don’t flush.

• For children under 6, use adult supervision

Inactive ingredients

- Water, Glycerin, Triethyl Citrate, Citrus Paradisi (Grapefruit) Peel Oil, Aloe Barbadensis Leaf Extract, Gamma-Undecalactone, Methylbenzyl Acetate, Neral, Ethyl Hydroxypyrone, Ethyl Butyrate, Furaneol, Grapefruit Mercaptan, Limonene

Purpose

Antiseptic

Uses

• Helps reduce bacteria on the skin.

• Recommended for repeated use.

Other Safety Information

• Do not use as a baby wipe

• Do not use in genital area or on damaged skin

Warnings

- For external use only
- Flammable, keep away from fire, sparks, and sources of ignition. Do not store above 104°F/40°C

When using this product

• Keep out of eyes

• In case of contact with eyes, flush thoroughly with water

Stop use and ask a doctor if irritation and redness develop and persist for more than 72 hours

Keep out of reach of children. If swallowed, get medical help or contact a Poison Control Center immediately.